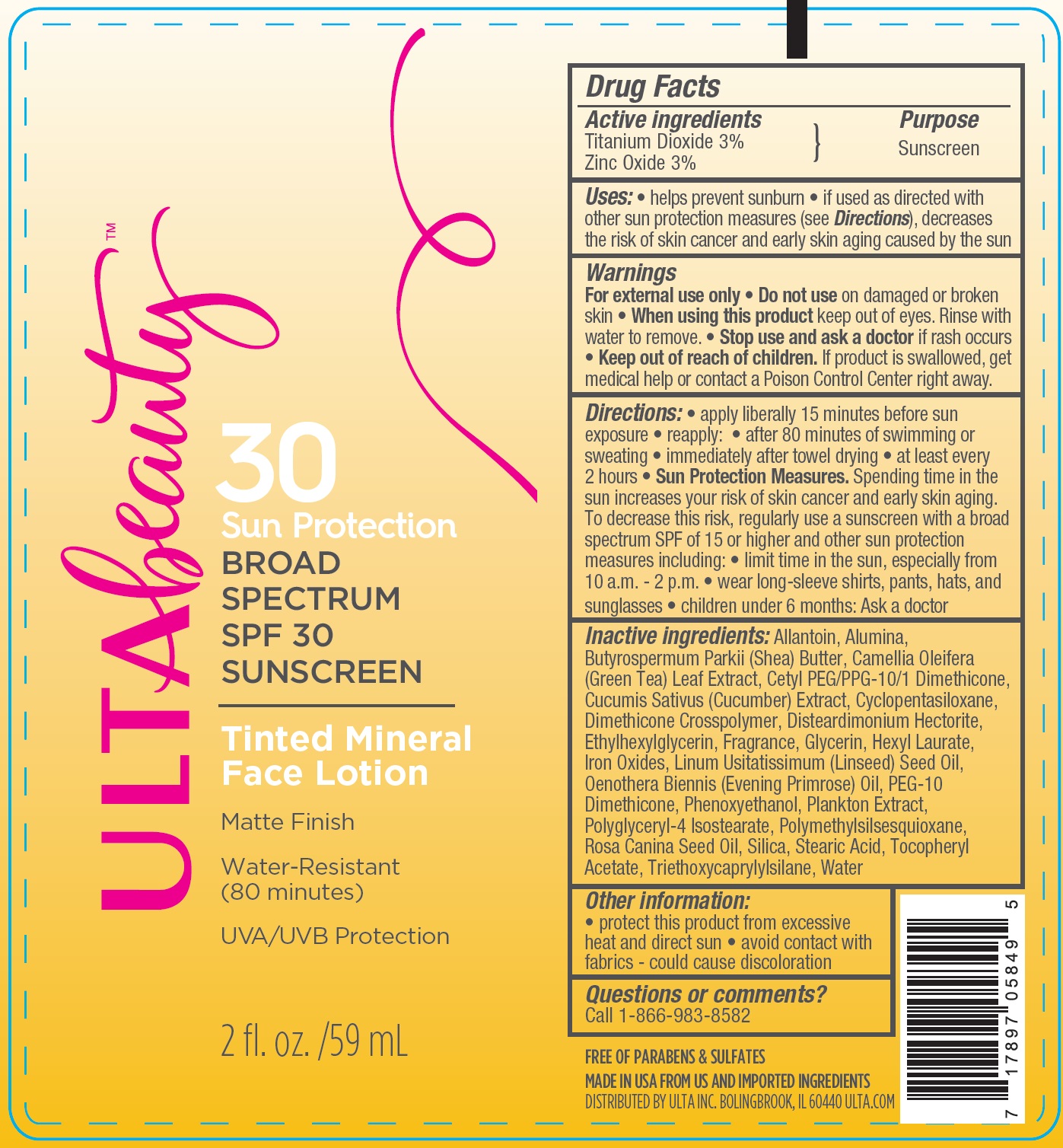 DRUG LABEL: Ulta Beauty
NDC: 58443-0245 | Form: LOTION
Manufacturer: Prime Enterprises Inc.
Category: otc | Type: HUMAN OTC DRUG LABEL
Date: 20200117

ACTIVE INGREDIENTS: TITANIUM DIOXIDE 31.38 mg/1 mL; ZINC OXIDE 31.38 mg/1 mL
INACTIVE INGREDIENTS: ROSA CANINA FRUIT OIL; SILICON DIOXIDE; EVENING PRIMROSE OIL; PHENOXYETHANOL; CYCLOMETHICONE 5; HEXYL LAURATE; PEG-10 DIMETHICONE (600 CST); POLYGLYCERYL-4 ISOSTEARATE; STEARIC ACID; ALUMINUM OXIDE; .ALPHA.-TOCOPHEROL ACETATE; ALLANTOIN; SHEA BUTTER; GLYCERIN; CETYL PEG/PPG-10/1 DIMETHICONE (HLB 2); CUCUMBER; GREEN TEA LEAF; DIMETHICONE CROSSPOLYMER (450000 MPA.S AT 12% IN CYCLOPENTASILOXANE); DISTEARDIMONIUM HECTORITE; FERRIC OXIDE RED; WATER; LINSEED OIL; TRIETHOXYCAPRYLYLSILANE; ETHYLHEXYLGLYCERIN; POLYMETHYLSILSESQUIOXANE (11 MICRONS)

Ulta Beauty SPF 30 Broad Spectrum Tinted Mineral Sunscreen

Active Ingredients

TItanium Dioxide 3%

Zinc Oxide 3%

Purpose

Sunscreen

Uses

- helps prevent sunburn
- if used as directed with other sun protection measures (see Directions), decreases the risk of skin cancer and early skin aging caused by the sun.

Warnings

For external use only.

Do not use on damaged or broken skin

When using this product keep out of eyes. Rinse with water to remove.

Stop use and ask a doctor if rash occurs

Keep out of reach of children. If product is swallowed, get medical help or contact a Poison Control Center right away.

Directions

- apply liberally 15 minutes before sun exposure
- reapply:
- after 80 minutes of swimming or sweating
- immediately after towel drying
- at least every 2 hours
- Sun Protection Measures. Spending time in the sun increases your risk of skin cancer and early skin aging. To decrease this risk, regularly use a sunscreen with broad spectrum SPF of 15 or higher and other sun protection measures including:
- limit time in the sun, especially from 10 a.m. – 2 p.m.
- wear long-sleeve shirts, pants, hats, and sunglasses
- children under 6 months: Ask a doctor

INACTIVE INGREDIENT

Allantoin, Alumina, Butyrospermum Parkii (Shea) Butter, Camellia Oleifera (Green Tea) Leaf Extract, Cetyl PEG/PPG-10/1 Dimethicone, Cucumis Sativus (Cucumber) Extract, Cyclopentasiloxane, Dimethicone Crosspolymer, Disteardimonium Hectorite, Ethylhexylglycerin, Fragrance, Glycerin, Hexyl Laurate, Iron Oxides, Linum Usitatissimum (Linseed) Seed Oil, Oenothera Biennis (Evening Primrose) Oil, PEG-10 Dimethicone, Phenoxyethanol, Plankton Extract, Polyglyceryl-4 Isostearate, Polymethylsilsesquioxane, Rosa Canina Fruit Oil, Silica, Stearic Acid, Tocopheryl Acetate, Triethoxycaprylylsilane, Water

Other Information

- protect this product from excessive heat and direct sun
- avoid contact with fabrics - could cause discoloration

Question or comments?

Call 1-866-983-8582